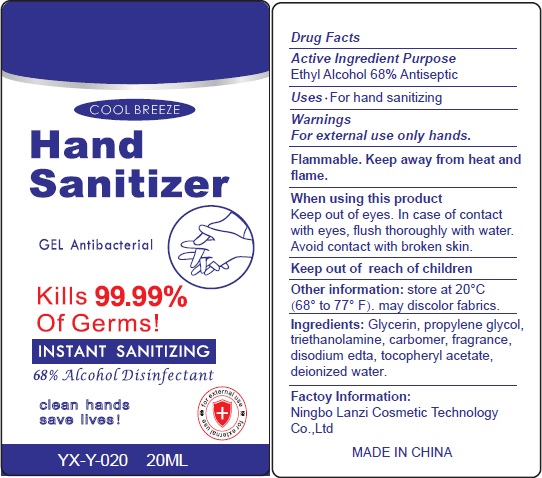 DRUG LABEL: HAND SANITIZER
NDC: 75613-008 | Form: GEL
Manufacturer: Ningbo Lanzi Cosmetic Technology Co., Ltd
Category: otc | Type: HUMAN OTC DRUG LABEL
Date: 20200522

ACTIVE INGREDIENTS: ALCOHOL 68 mL/100 mL
INACTIVE INGREDIENTS: WATER; PROPYLENE GLYCOL; EDETATE DISODIUM; TROLAMINE; .ALPHA.-TOCOPHEROL ACETATE, D-; GLYCERIN

HAND SANITIZER

Active ingredient

Ethyl Alcohol 68%

Purpose

Antiseptic

Use

For hand sanitizing

Warnings

For external use only.

Flammable.Keep away from heat and flame.

When using this product

keep out of eyes. In case of contact with eyes, flush thoroughly with water.

Avoid contact with broken skin.

Stop use and ask a doctor if

rash occurs.

Keep out of reach of children.

If swallowed, get medical help or contact a Poison Control Center right away.

Directions

Wet hands thoroughly with product and rub hands together briskly until dry.

Inactive ingredients

Glycerin,Propylene Glycol, Triethanolamine, Carbomer, Fragrance, Disodium Edta, Tocopheryl Acetate, Deionized Water